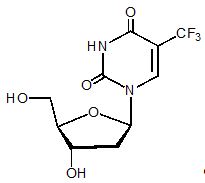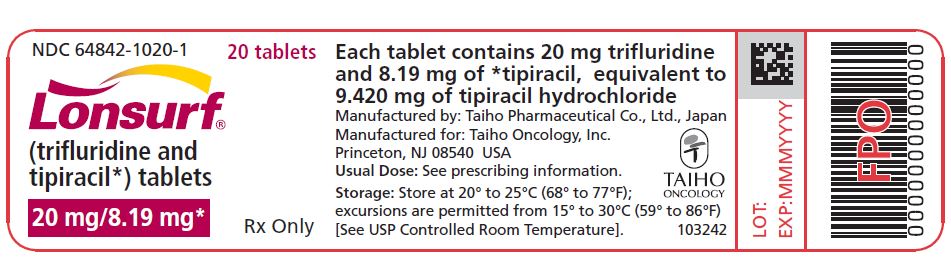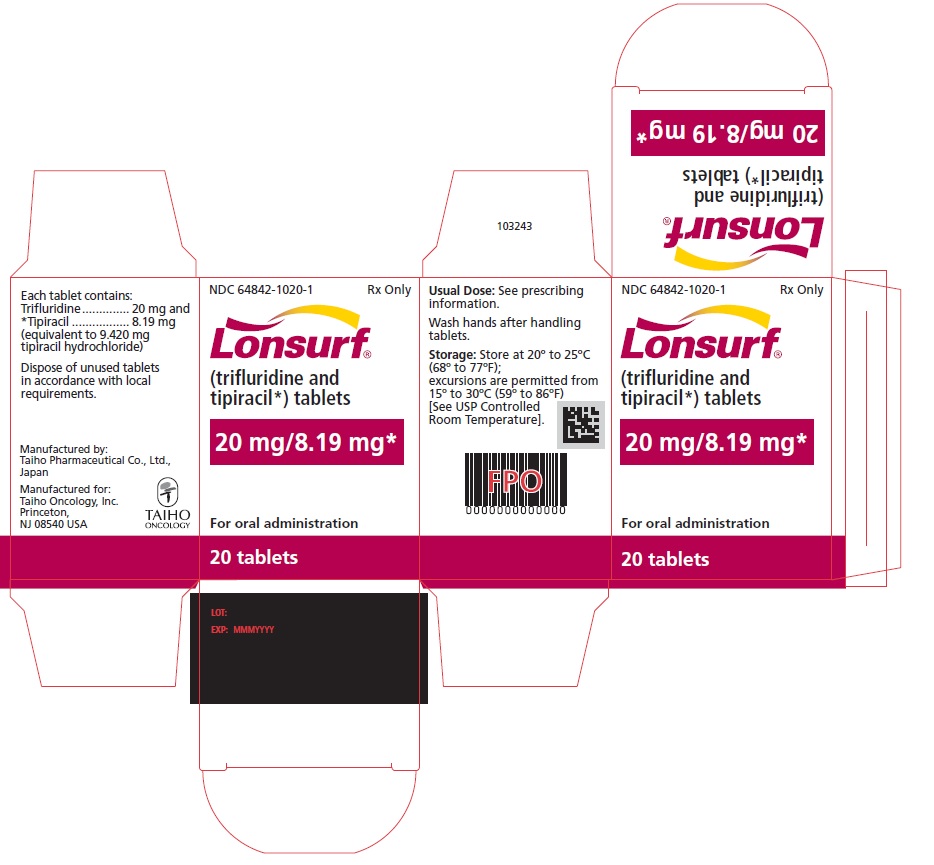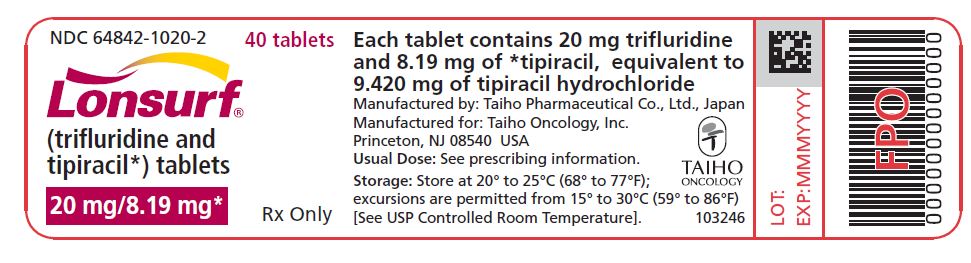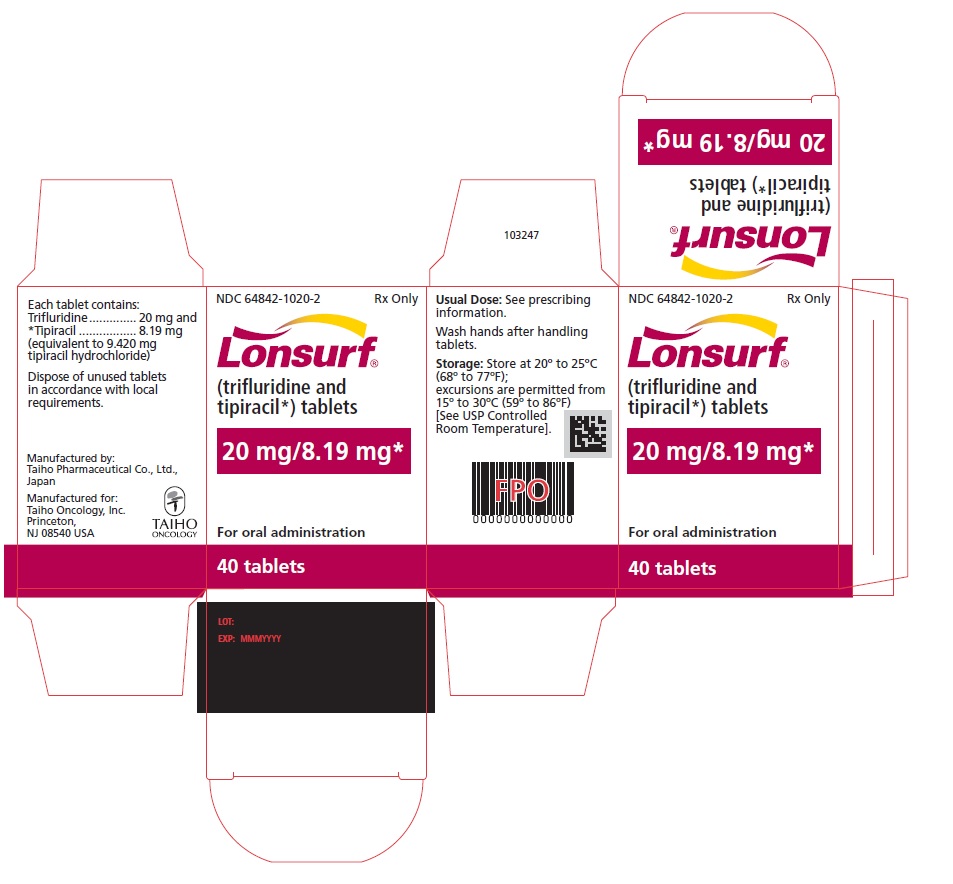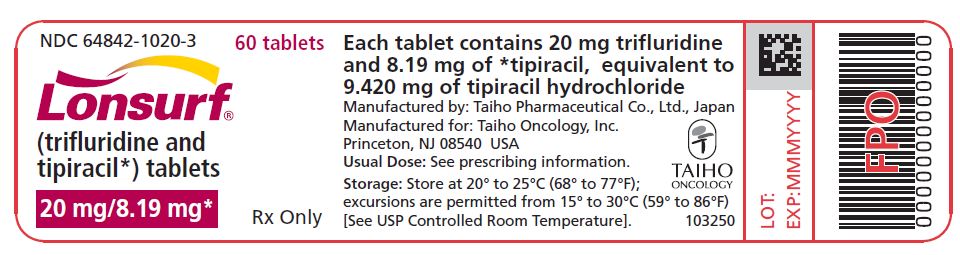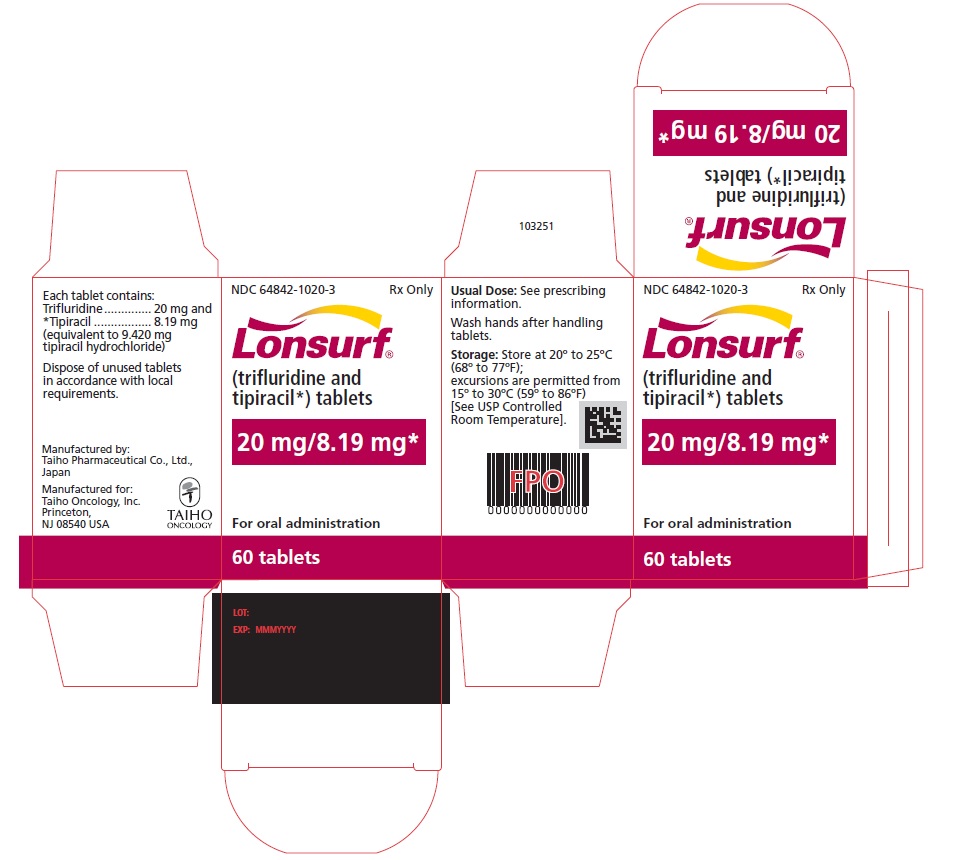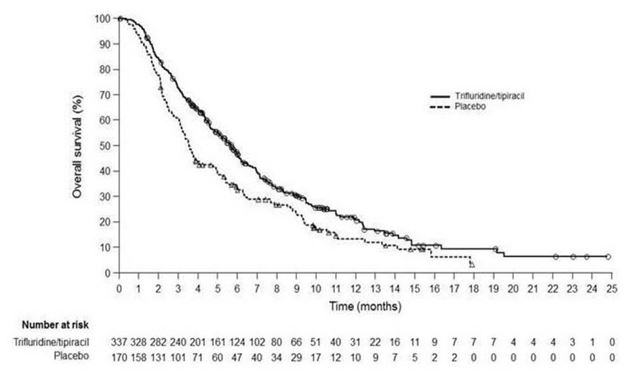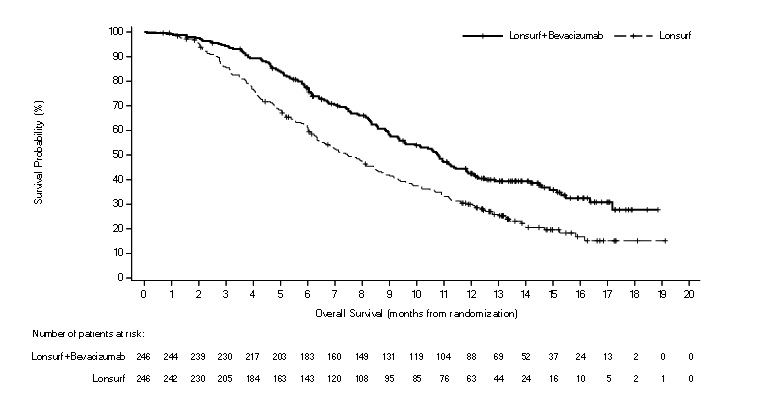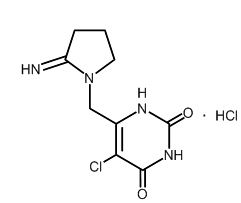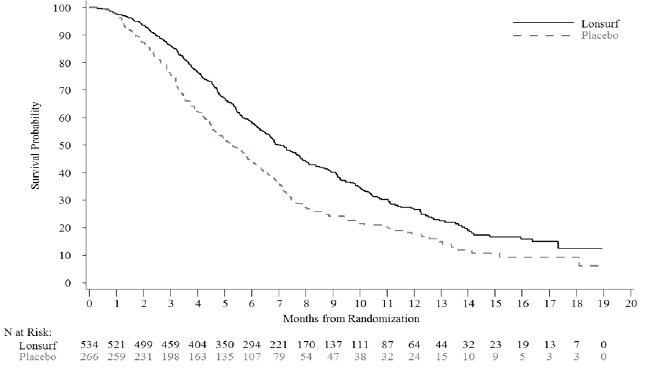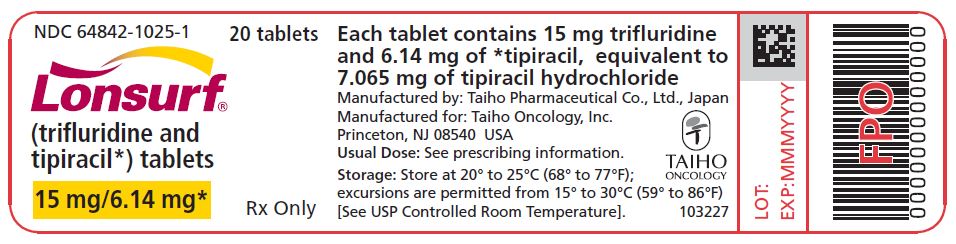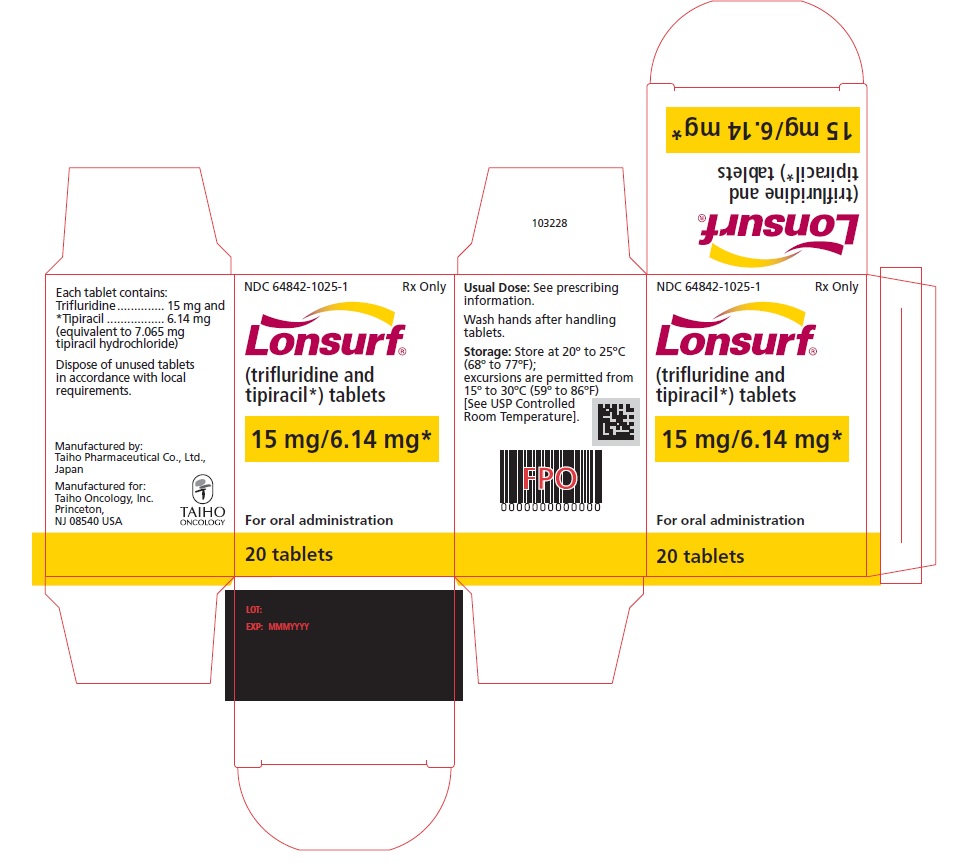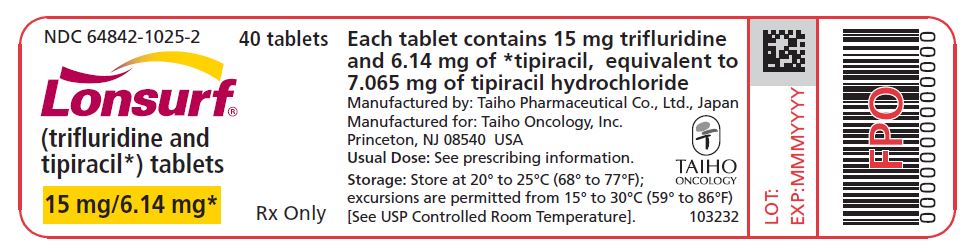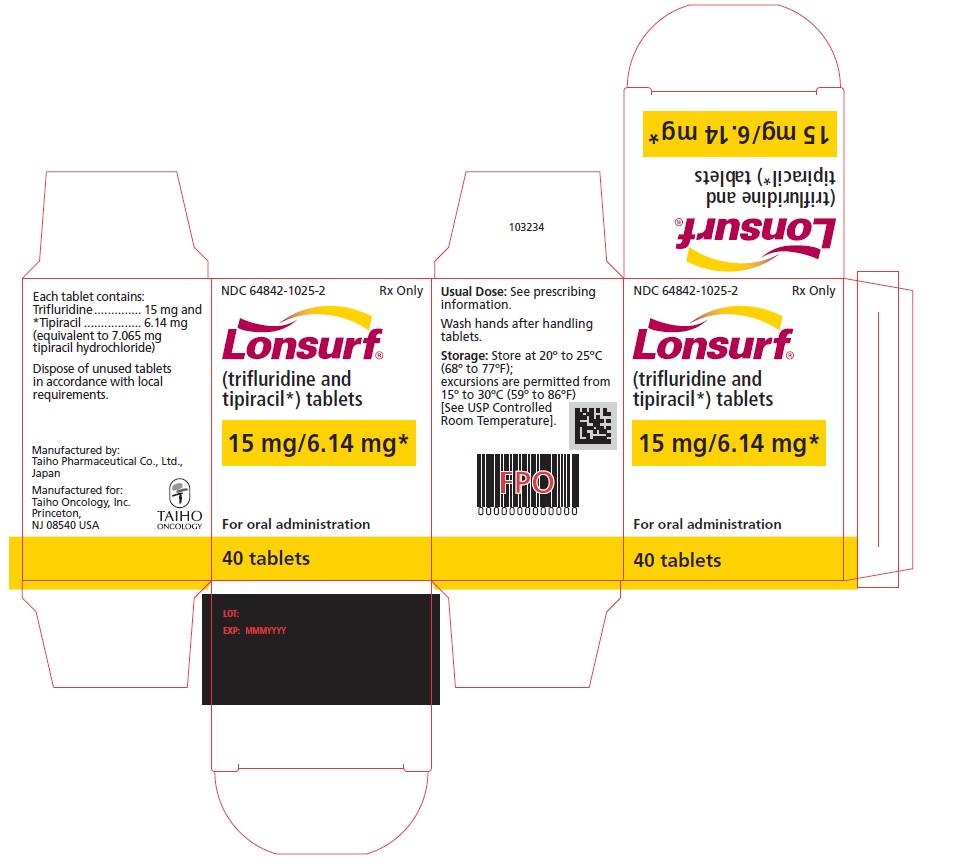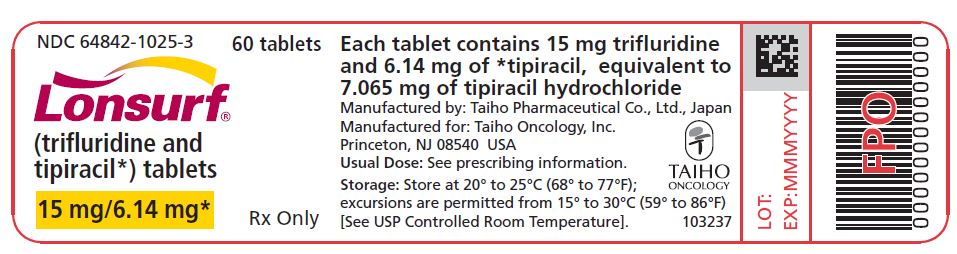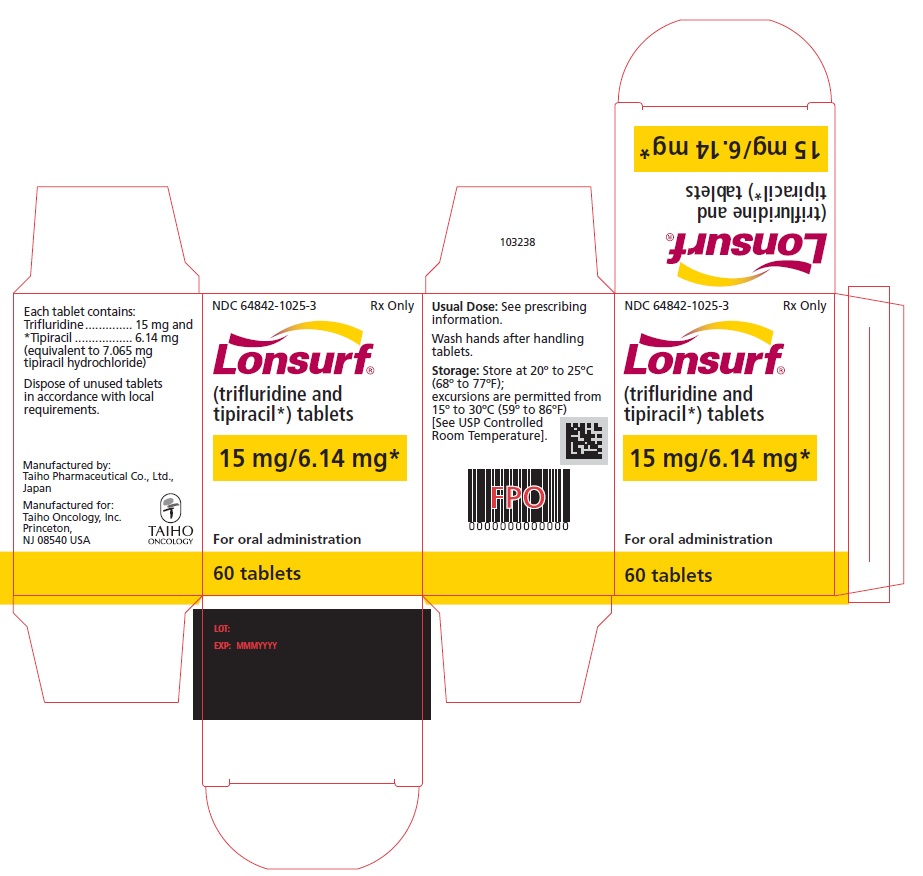 DRUG LABEL: LONSURF
NDC: 64842-1025 | Form: TABLET, FILM COATED
Manufacturer: Taiho Pharmaceutical Co., Ltd.
Category: prescription | Type: HUMAN PRESCRIPTION DRUG LABEL
Date: 20251105

ACTIVE INGREDIENTS: TRIFLURIDINE 15 mg/1 1; TIPIRACIL HYDROCHLORIDE 6.14 mg/1 1
INACTIVE INGREDIENTS: LACTOSE MONOHYDRATE 90.735 mg/1 1; STARCH, CORN 6.000 mg/1 1; STEARIC ACID 1.200 mg/1 1; HYPROMELLOSE, UNSPECIFIED 2.100 mg/1 1; POLYETHYLENE GLYCOL, UNSPECIFIED 0.300 mg/1 1; TITANIUM DIOXIDE 0.300 mg/1 1; MAGNESIUM STEARATE 0.003 mg/1 1; ALCOHOL; BUTYL ALCOHOL

HIGHLIGHTS OF PRESCRIBING INFORMATION

These highlights do not include all the information needed to use LONSURF safely and effectively. See full prescribing information for LONSURF.
LONSURF (trifluridine and tipiracil) tablets, for oral use
Initial U.S. Approval: 2015

RECENT MAJOR CHANGES

Indications and Usage (1.1) | 8/2023
Dosage and Administration (2) | 8/2023
Warnings and Precaution (5.1) | 8/2023

1 INDICATIONS AND USAGE

LONSURF is a combination of trifluridine, a nucleoside metabolic inhibitor, and tipiracil, a thymidine phosphorylase inhibitor, indicated for the treatment of adult patients with:

- metastatic colorectal cancer as a single agent or in combination with bevacizumab who have been previously treated with fluoropyrimidine-, oxaliplatin- and irinotecan-based chemotherapy, an anti-VEGF biological therapy, and if RAS wild-type, an anti-EGFR therapy. (1.1)
- metastatic gastric or gastroesophageal junction adenocarcinoma previously treated with at least two prior lines of chemotherapy that included a fluoropyrimidine, a platinum, either a taxane or irinotecan, and if appropriate, HER2/neu-targeted therapy. (1.2)

2 DOSAGE AND ADMINISTRATION

- Recommended Dosage: 35 mg/m^2/dose orally twice daily with food on Days 1 through 5 and Days 8 through 12 of each 28-day cycle. (2.1)

3 DOSAGE FORMS AND STRENGTHS

Tablets:

- 15 mg trifluridine/6.14 mg tipiracil (3)
- 20 mg trifluridine/8.19 mg tipiracil (3)

4 CONTRAINDICATIONS

None. (4)

5 WARNINGS AND PRECAUTIONS

- Severe Myelosuppression: Obtain complete blood counts prior to and on Day 15 of each cycle. Withhold and resume at next lower LONSURF dosage as recommended. (2.1, 5.1)
- Embryo-Fetal Toxicity: Can cause fetal harm. Advise females of reproductive potential of the potential risk to a fetus and to use effective contraception. (5.2, 8.1, 8.3)

6 ADVERSE REACTIONS

The most common adverse reactions or laboratory abnormalities for single agent LONSURF (≥10%) are neutropenia, anemia, thrombocytopenia, fatigue, nausea, decreased appetite, diarrhea, vomiting, abdominal pain, and pyrexia. (6.1)

The most common adverse reactions or laboratory abnormalities for LONSURF in combination with bevacizumab (≥20%) are neutropenia, anemia, thrombocytopenia, fatigue, nausea, increased AST, increased ALT, increased alkaline phosphatase, decreased sodium, diarrhea, abdominal pain, and decreased appetite. (6.1)

To report SUSPECTED ADVERSE REACTIONS, contact Taiho Oncology, Inc. at 1-844-878-2446 or FDA at 1-800-FDA-1088 or www.fda.gov/medwatch.

8 USE IN SPECIFIC POPULATIONS

- Lactation: Advise not to breastfeed. (8.2)
- Geriatric Use: For LONSURF as a single agent, Grade 3 or 4 neutropenia, Grade 3 anemia and Grade 3 or 4 thrombocytopenia occurred more commonly in patients 65 years or older. (8.5) For LONSURF in combination with bevacizumab Grade 3 or 4 neutropenia and Grade 3 or 4 thrombocytopenia occurred more commonly in patients 65 years or older. (8.5)
- Hepatic Impairment: Do not initiate LONSURF in patients with baseline moderate or severe hepatic impairment. (8.7)
- Renal Impairment: Reduce LONSURF dose in patients with severe renal impairment. (8.6)

FULL PRESCRIBING INFORMATION

1 INDICATIONS AND USAGE

1.1 Metastatic Colorectal Cancer

LONSURF, as a single agent or in combination with bevacizumab, is indicated for the treatment of adult patients with metastatic colorectal cancer previously treated with fluoropyrimidine-, oxaliplatin- and irinotecan-based chemotherapy, an anti-VEGF biological therapy, and if RAS wild-type, an anti-EGFR therapy.

1.2 Metastatic Gastric Cancer

LONSURF is indicated for the treatment of adult patients with metastatic gastric or gastroesophageal junction adenocarcinoma previously treated with at least two prior lines of chemotherapy that included a fluoropyrimidine, a platinum, either a taxane or irinotecan, and if appropriate, HER2/neu-targeted therapy.

2 DOSAGE AND ADMINISTRATION

2.1 Recommended Dosage

The recommended dosage of LONSURF as a single agent or in combination with bevacizumab is 35 mg/m^2 up to a maximum of 80 mg per dose (based on the trifluridine component) orally twice daily with food on Days 1 through 5 and Days 8 through 12 of each 28-day cycle until disease progression or unacceptable toxicity. Round dose to the nearest 5 mg increment.

Refer to the Prescribing Information for bevacizumab dosing information.

Instruct patients to swallow LONSURF tablets whole.
Instruct patients not to retake doses of LONSURF that are vomited or missed and to continue with the next scheduled dose.
LONSURF is a cytotoxic drug. Follow applicable special handling and disposal procedures.^1
Table 1 shows the calculated initial daily dose based on body surface area (BSA).

Table 1: Recommended Dosage According to Body Surface Area (BSA)
BSA (m2) | Total daily dose (mg) | Dose (mg) administered twice daily | Tablets per dose
BSA (m2) | Total daily dose (mg) | Dose (mg) administered twice daily | 15 mg | 20 mg
< 1.07 | 70 | 35 | 1 | 1
1.07 – 1.22 | 80 | 40 | 0 | 2
1.23 – 1.37 | 90 | 45 | 3 | 0
1.38 – 1.52 | 100 | 50 | 2 | 1
1.53 – 1.68 | 110 | 55 | 1 | 2
1.69 – 1.83 | 120 | 60 | 0 | 3
1.84 – 1.98 | 130 | 65 | 3 | 1
1.99 – 2.14 | 140 | 70 | 2 | 2
2.15 – 2.29 | 150 | 75 | 1 | 3
≥2.30 | 160 | 80 | 0 | 4

2.2 Dosage Modifications for Adverse Reactions

Obtain complete blood cell counts prior to and on Day 15 of each cycle [see Warnings and Precautions (5.1)].

Do not initiate the cycle of LONSURF until:

- Absolute neutrophil count (ANC) greater than or equal to 1,500/mm^3 or febrile neutropenia is resolved
- Platelets greater than or equal to 75,000/mm^3
- Grade 3 or 4 non-hematological adverse reactions are resolved to Grade 0 or 1

Within a treatment cycle, withhold LONSURF for any of the following:

- Absolute neutrophil count (ANC) less than 500/mm^3 or febrile neutropenia
- Platelets less than 50,000/mm^3
- Grade 3 or 4 non-hematologic adverse reaction

After recovery, resume LONSURF after reducing the dose by 5 mg/m^2/dose from the previous dose, if the following occur:

- Febrile neutropenia
- Uncomplicated Grade 4 neutropenia (which has recovered to greater than or equal to 1,500/mm^3) or thrombocytopenia (which has recovered to greater than or equal to 75,000/mm^3) that results in more than 1 week delay in start of next cycle
- Non-hematologic Grade 3 or Grade 4 adverse reaction except for Grade 3 nausea and/or vomiting controlled by antiemetic therapy or Grade 3 diarrhea responsive to antidiarrheal medication

A maximum of 3 dose reductions are permitted. Permanently discontinue LONSURF in patients who are unable to tolerate a dose of 20 mg/m^2 orally twice daily. Do not escalate LONSURF dosage after it has been reduced.

Refer to the bevacizumab prescribing information for dose modifications for adverse reactions associated with bevacizumab.

2.3 Recommended Dosage for Renal Impairment

Severe Renal Impairment

In patients with severe renal impairment [creatinine clearance (CLcr) of 15 to 29 mL/min as determined by the Cockcroft-Gault formula], the recommended dosage is 20 mg/m^2 (based on the trifluridine component) orally twice daily with food on Days 1 through 5 and Days 8 through 12 of each 28-day cycle (Table 2) [see Use in Specific Populations (8.6) and Clinical Pharmacology (12.3)]. Reduce dose to 15 mg/m^2 twice daily in patients with severe renal impairment who are unable to tolerate a dose of 20 mg/m^2 twice daily (Table 2). Permanently discontinue LONSURF in patients who are unable to tolerate a dose of 15 mg/m^2 twice daily.

Table 2: Recommended Dosage for Severe Renal Impairment According to BSA
BSA (m^2) | Total daily dose (mg) | Dose (mg) administered twice daily | Tablets per dose
BSA (m^2) | Total daily dose (mg) | Dose (mg) administered twice daily | 15 mg | 20 mg
For a dose of 20 mg/m^2 twice daily:
< 1.14 | 40 | 20 | 0 | 1
1.14 – 1.34 | 50 | 25 [For a total daily dose of 50 mg, instruct patients to take 1 x 20-mg tablet in the morning and 2 x 15-mg tablets in the evening.] | 2 in the evening | 1 in the morning
1.35 – 1.59 | 60 | 30 | 2 | 0
1.60 – 1.94 | 70 | 35 | 1 | 1
1.95 – 2.09 | 80 | 40 | 0 | 2
2.10 – 2.34 | 90 | 45 | 3 | 0
≥ 2.35 | 100 | 50 | 2 | 1
For a dose of 15 mg/m^2 twice daily:
< 1.15 | 30 | 15 | 1 | 0
1.15 – 1.49 | 40 | 20 | 0 | 1
1.50 – 1.84 | 50 | 25 | 2 in the evening | 1 in the morning
1.85 – 2.09 | 60 | 30 | 2 | 0
2.10 – 2.34 | 70 | 35 | 1 | 1
≥ 2.35 | 80 | 40 | 0 | 2

3 DOSAGE FORMS AND STRENGTHS

Tablets:

- 15 mg trifluridine/6.14 mg tipiracil: white, biconvex, round, film-coated, imprinted with ‘15’ on one side, and ‘102’ and ‘15 mg’ on the other side, in gray ink.
- 20 mg trifluridine/8.19 mg tipiracil: pale red, biconvex, round, film-coated, imprinted with ‘20’ on one side, and ‘102’ and ‘20 mg’ on the other side, in gray ink.

4 CONTRAINDICATIONS

None.

5 WARNINGS AND PRECAUTIONS

5.1 Severe Myelosuppression

In the 1114 patients who received LONSURF as a single agent, LONSURF caused severe or life-threatening myelosuppression (Grade 3-4) consisting of neutropenia (38%), anemia (17%), thrombocytopenia (4%) and febrile neutropenia (3%). Three patients (0.3%) died due to neutropenic infection/sepsis; four other patients (0.5%) died due to septic shock. A total of 14% of patients received granulocyte-colony stimulating factors.

In the 246 patients who received LONSURF in combination with bevacizumab, LONSURF caused severe or life-threatening myelosuppression (Grade 3-4) consisting of neutropenia (52%), anemia (5%), thrombocytopenia (4%) and febrile neutropenia (0.4%). One patient (0.4%) died due to abdominal sepsis and two other patients (0.8%) died due to septic shock. A total of 29% of patients received granulocyte-colony stimulating factors. Obtain complete blood counts prior to and on Day 15 of each cycle of LONSURF and more frequently as clinically indicated. Withhold LONSURF for severe myelosuppression and resume at the next lower dosage [see Dosage and Administration (2.2)].

5.2 Embryo-Fetal Toxicity

Based on animal studies and its mechanism of action, LONSURF can cause fetal harm when administered to a pregnant woman. Trifluridine/tipiracil caused embryo-fetal lethality and embryo-fetal toxicity in pregnant rats when orally administered during gestation at dosage levels resulting in exposures lower than those achieved at the recommended dosage of 35 mg/m^2 twice daily. Advise pregnant women of the potential risk to the fetus. Advise females of reproductive potential to use an effective method of contraception during treatment with LONSURF and for at least 6 months after the final dose [see Use in Specific Populations (8.1, 8.3)].

6 ADVERSE REACTIONS

The following clinically significant adverse reactions are described elsewhere in the labeling:

- Severe Myelosuppression [see Warnings and Precautions (5.1)]

6.1 Clinical Trials Experience

Because clinical trials are conducted under widely varying conditions, adverse reaction rates observed in the clinical trials of a drug cannot be directly compared to rates in the clinical trials of another drug and may not reflect the rates observed in practice.

The data described in the WARNINGS AND PRECAUTIONS section and below reflect exposure to LONSURF at the recommended dose in 533 patients with metastatic colorectal cancer in RECOURSE, 246 patients with metastatic colorectal cancer treated with LONSURF as monotherapy in SUNLIGHT and 335 patients with metastatic gastric cancer in TAGS. Among the 1114 patients who received LONSURF as a single agent, 12% were exposed for 6 months or longer and 1% were exposed for 12 months or longer. The most common adverse reactions or laboratory abnormalities (≥10%) were neutropenia, anemia, thrombocytopenia, fatigue, nausea, decreased appetite, diarrhea, vomiting, abdominal pain, and pyrexia.

Among the 246 patients with metastatic colorectal cancer treated with LONSURF in combination with bevacizumab in SUNLIGHT, 39% were exposed for 6 months or longer, and 14% were exposed for 12 months or longer. The most common adverse reactions or laboratory abnormalities (≥20%) were neutropenia, anemia, thrombocytopenia, fatigue, nausea, increased AST, increased ALT, increased alkaline phosphatase, decreased sodium, diarrhea, abdominal pain, and decreased appetite.

Metastatic Colorectal Cancer

LONSURF as a single agent

The safety of LONSURF was evaluated in RECOURSE, a randomized (2:1), double-blind, placebo-controlled trial in patients with previously treated metastatic colorectal cancer [see Clinical Studies (14.1)]. Patients received LONSURF 35 mg/m^2/dose (n=533) or placebo (n=265) twice daily on Days 1 through 5 and Days 8 through 12 of each 28-day cycle. In RECOURSE, 12% of patients received LONSURF for more than 6 months and 1% of patients received LONSURF for more than 1 year.

The study population characteristics were: median age 63 years; 61% male; 57% White, 35% Asian, and 1% Black.

The most common adverse reactions or laboratory abnormalities (≥10% in incidence) in patients treated with LONSURF at a rate that exceeds the rate in patients receiving placebo were anemia, neutropenia, asthenia/fatigue, nausea, thrombocytopenia, decreased appetite, diarrhea, vomiting, abdominal pain, and pyrexia.

In RECOURSE, 3.6% of patients discontinued LONSURF for an adverse reaction and 14% of patients required a dose reduction. The most common adverse reactions or laboratory abnormalities leading to dose reduction were neutropenia, anemia, febrile neutropenia, fatigue, and diarrhea.

Table 3 and Table 4 list the adverse reactions and laboratory abnormalities (graded using CTCAE v4.03), respectively, observed in RECOURSE.

Table 3: Adverse Reactions (≥5%) in Patients Receiving LONSURF and at a Higher Incidence (>2%) than in Patients Receiving Placebo in RECOURSE
Adverse Reactions | LONSURF (N=533) |  | Placebo (N=265)
Adverse Reactions | All Grades (%) | Grades 3-4 [No Grade 4 definition for nausea, abdominal pain, or fatigue in National Cancer Institute Common Terminology] (%) | All Grades (%) | Grades 3-4 (%)
General
Asthenia/fatigue | 52 | 7 | 35 | 9
Pyrexia | 19 | 1.3 | 14 | 0.4
Gastrointestinal
Nausea | 48 | 1.9 | 24 | 1.1
Diarrhea | 32 | 3 | 12 | 0.4
Vomiting | 28 | 2.1 | 14 | 0.4
Abdominal pain | 21 | 2.4 | 19 | 3.8
Stomatitis | 8 | 0.4 | 6 | 0
Metabolism and nutrition
Decreased appetite | 39 | 3.6 | 29 | 4.9
Infections [Incidence reflects 64 preferred terms in the Infections and Infestations system organ class.] | 27 | 7 | 16 | 4.9
Nervous system
Dysgeusia | 7 | 0 | 2.3 | 0
Skin and subcutaneous tissue
Alopecia | 7 | 0 | 1.1 | 0

Table 4: Select Laboratory Abnormalities in RECOURSE
Laboratory Parameter [Worst Grade at least one grade higher than baseline, with percentages based on number of patients with post-baseline samples, which may be <533 (LONSURF) or 265 (placebo)] | LONSURF |  | Placebo
Laboratory Parameter [Worst Grade at least one grade higher than baseline, with percentages based on number of patients with post-baseline samples, which may be <533 (LONSURF) or 265 (placebo)] | All Grades (%) | Grades 3-4 (%) | All Grades (%) | Grades 3-4 (%)
Hematologic
Anemia [One Grade 4 anemia adverse reaction based on clinical criteria was reported] | 77 | 18 | 33 | 3
Neutropenia | 67 | 38 | 0.8 | 0
Thrombocytopenia | 42 | 5 | 8 | 0.4

In RECOURSE, pulmonary emboli occurred more frequently in LONSURF-treated patients (2%) compared to no patients on placebo.

LONSURF in combination with bevacizumab

The safety of LONSURF in combination with bevacizumab was evaluated in SUNLIGHT, an international, randomized, open label study in patients with previously treated metastatic colorectal cancer [see Clinical Studies (14.1)].

The study population characteristics were: median age 63 years (20 to 90 years); 52% male; 88% White, 1.4% Black, 0.2% Asian, 0.2% American Indian or Alaska Native, and 9.6% were unknown; and baseline ECOG performance status 0 (46%), 1 (54%), or 2 (0.2%).

Serious adverse reactions occurred in 25% of patients. The most frequent serious adverse reactions (≥2%) were intestinal obstruction (2.8%), and COVID-19 (2%). Fatal adverse reactions occurred in 1.2% of patients who received LONSURF in combination with bevacizumab, including rectal fistula (0.4%), bowel perforation (0.4%) and atrial fibrillation (0.4%).

Permanent treatment discontinuation due to an adverse reaction occurred in 13% of patients. The adverse reaction which resulted in permanent treatment discontinuation in ≥2% of patients was fatigue.

Dosage reductions due to an adverse reaction or laboratory abnormality occurred in 7% of patients. At least one dose reduction in 3.7% of patients was required for neutropenia.

Dosage interruptions due to an adverse reaction occurred in 11% of patients who received LONSURF in combination with bevacizumab. The adverse reaction that required dosage interruption in ≥2% of patients was nausea.

The most common adverse reactions or laboratory abnormalities (≥20% in incidence) in patients treated with LONSURF in combination with bevacizumab were neutropenia, anemia, thrombocytopenia, fatigue, nausea, increased aspartate aminotransferase, increased alanine aminotransferase, increased alkaline phosphatase, decreased sodium, diarrhea, abdominal pain, and decreased appetite. Table 5 and Table 6 list the adverse reactions and laboratory abnormalities, respectively, observed in SUNLIGHT.

Table 5: Adverse Reactions (≥5%) in SUNLIGHT
Adverse Reactions | LONSURF + Bevacizumab (N=246) (%) |  | LONSURF (N=246) (%)
Adverse Reactions | All Grades | Grade 3 or 4 | All Grades | Grade 3 or 4
Gastrointestinal disorders
Nausea | 37 | 1.6 | 27 | 1.6
Diarrhea [Represents a composite of multiple related terms] | 21 | 1.2 | 19 | 2.4
Abdominal pain | 20 | 2.8 | 18 | 3.7
Vomiting | 19 | 0.8 | 15 | 1.6
Stomatitis | 13 | <0.4 | 4.1 | 0
Constipation | 11 | 0 | 11 | 0.8
General disorders and administration site conditions
Fatigue | 45 | 5 | 37 | 8
Pyrexia | 4.9 | 0 | 6 | 0.4
Infections and infestations | 31 | 8 | 24 | 8
Metabolism and nutrition disorders
Decreased appetite | 20 | <0.8 | 15 | 1.2
Musculoskeletal and connective tissue disorders
Musculoskeletal pain | 18 | 1.2 | 11 | 2
Nervous system disorder
Headache | 8 | 0 | 3.7 | 0
Vascular disorders
Hypertension | 11 | 6 | 2 | 1.2
Hemorrhage | 10 | 1.2 | 3.7 | 0.8
Renal and urinary disorders
Proteinuria | 6 | 0.8 | 1.2 | 0

Table 6: Select Laboratory Abnormalities (≥10%) in SUNLIGHT
Laboratory parameters | LONSURF + Bevacizumab [Each test incidence is based on the number of patients who had both baseline and at least one on-study laboratory measurement available: LONSURF + bevacizumab group (n=242 patients) and LONSURF group (range: 240 to 242 patients).] |  | LONSURF
 | All Grades (%) | Grade 3 or 4 (%) | All Grades (%) | Grade 3 or 4 (%)
Hematology
Neutrophils decreased | 80 | 52 | 68 | 39
Hemoglobin decreased | 68 | 5 | 73 | 11
Platelets decreased | 54 | 4.1 | 29 | 0.8
Chemistry
Aspartate aminotransferase increased | 34 | 2.1 | 28 | 1.2
Alanine aminotransferase increased | 33 | 3.3 | 23 | 0.4
Alkaline phosphatase increased | 31 | 0.8 | 36 | 1.2
Sodium decreased | 25 | 2.1 | 20 | 3.3
Potassium increased | 17 | 0 | 15 | 0
Potassium decreased | 12 | 0.8 | 12 | 2.5
Creatinine increased | 12 | 0.8 | 15 | 0

Metastatic Gastric Cancer

The safety of LONSURF was evaluated in TAGS, an international, randomized (2:1), double-blind, placebo-controlled trial in patients with metastatic gastric or gastroesophageal junction (GEJ) adenocarcinoma who were previously treated with at least 2 prior chemotherapy regimens for advanced disease [see Clinical Studies (14.2)]. Previous treatments must have included a fluoropyrimidine, a platinum, and either a taxane or irinotecan. Patients with HER2/neu-positive tumors must have received prior HER2/neu-targeted therapy, if available. Adjuvant chemotherapy could be counted as one prior regimen in patients who had recurrence during or within 6 months of completion of the adjuvant chemotherapy. Patients received LONSURF 35 mg/m^2/dose (n=335) or placebo (n=168) twice daily on Days 1 through 5 and Days 8 through 12 of each 28-day cycle with best supportive care. In TAGS, 10% of patients received LONSURF for more than 6 months and 0.9% of patients received LONSURF for more than 1 year.

The study population characteristics were: median age 63 years (24 to 89 years); 73% male; 70% White, 16% Asian, and 1% Black.

The most common adverse reactions or laboratory abnormalities (≥10% in incidence) in patients treated with LONSURF at a rate that exceeds the rate in patients receiving placebo were neutropenia, anemia, nausea, decreased appetite, thrombocytopenia, vomiting, and diarrhea.

In TAGS, 13% of patients discontinued LONSURF for an adverse reaction and 11% of patients required a dose reduction. The most common adverse reactions or laboratory abnormalities leading to dose reduction were neutropenia, anemia, febrile neutropenia, and diarrhea.

Table 7 and Table 8 list the adverse reactions and laboratory abnormalities (graded using CTCAE v4.03), respectively, observed in TAGS.

Table 7: Adverse Reactions (≥5%) in Patients Receiving LONSURF and at a Higher Incidence (>2%) than in Patients Receiving Placebo in TAGS
Adverse Reactions | LONSURF (N=335) |  | Placebo (N=168)
Adverse Reactions | All Grades (%) | Grades 3-4 [No Grade 4 definition for nausea or fatigue in NCI CTCAE, version 4.03.] (%) | All Grades (%) | Grades 3-4 (%)
Gastrointestinal
Nausea | 37 | 3 | 32 | 3
Vomiting | 25 | 4 | 20 | 2
Diarrhea | 23 | 3 | 14 | 2
Metabolism and nutrition
Decreased appetite | 34 | 9 | 31 | 7
Infections [Incidence reflects 46 preferred terms in the Infections and Infestations system organ class.] | 23 | 5 | 16 | 5

Table 8: Laboratory Abnormalities in TAGS
Laboratory Parameter [Worst Grade at least one Grade higher than baseline, with percent based on number of patients with post-baseline samples which may be <335 (LONSURF) or 168 (placebo)] | LONSURF |  | Placebo
Laboratory Parameter [Worst Grade at least one Grade higher than baseline, with percent based on number of patients with post-baseline samples which may be <335 (LONSURF) or 168 (placebo)] | All Grades (%) | Grades 3-4 (%) | All Grades (%) | Grades 3-4 (%)
Hematologic
Neutropenia | 66 | 38 | 4 | 0
Anemia [Anemia: No Grade 4 definition in CTCAE, v4.03] | 63 | 19 | 38 | 7
Thrombocytopenia | 34 | 6 | 9 | 0

In TAGS, pulmonary emboli occurred more frequently in LONSURF-treated patients (3.1%) compared to 1.8% for patients on placebo.

Additional Clinical Experience

Interstitial lung disease was reported in 15 (0.2%) patients, 3 of which were fatal, among approximately 7,000 patients exposed to LONSURF in clinical studies and clinical practice settings in Asia.

8 USE IN SPECIFIC POPULATIONS

8.1 Pregnancy

Risk Summary

Based on animal data and its mechanism of action [see Clinical Pharmacology (12.2)], LONSURF can cause fetal harm. LONSURF caused embryo-fetal lethality and embryo-fetal toxicity in pregnant rats when given during gestation at doses resulting in exposures lower than or similar to human exposures at the recommended clinical dose (see Data). There are no available data on LONSURF use in pregnant women. Advise pregnant women of the potential risk to a fetus.

In the U.S. general population, the estimated background risk of major birth defects and miscarriage in clinically recognized pregnancies is 2-4% and 15-20%, respectively.

Data

Animal Data

Trifluridine/tipiracil was administered orally once daily to female rats during organogenesis at dose levels of 15, 50, and 150 mg/kg [trifluridine (FTD) equivalent]. Decreased fetal weight was observed at FTD doses ≥50 mg/kg (approximately 0.33 times the FTD exposure at the clinical dose of 35 mg/m^2 twice daily). At the FTD dose of 150 mg/kg (approximately 0.92 times the FTD exposure at the clinical dose of 35 mg/m^2 twice daily) embryolethality and structural anomalies (kinked tail, cleft palate, ectrodactyly, anasarca, alterations in great vessels, and skeletal anomalies) were observed.

8.2 Lactation

Risk Summary

There are no data on the presence of trifluridine, tipiracil or its metabolites in human milk or its effects on the breastfed child or on milk production. In nursing rats, trifluridine and tipiracil or their metabolites were present in breast milk (see Data). Because of the potential for serious adverse reactions in breastfed children, advise women not to breastfeed during treatment with LONSURF and for 1 day following the final dose.

Data

Radioactivity was excreted in the milk of nursing rats dosed with trifluridine/tipiracil containing ^14C-FTD or ^14C-tipiracil (TPI). Levels of FTD-derived radioactivity were as high as approximately 50% of the exposure in maternal plasma an hour after dosing with trifluridine/tipiracil and were approximately the same as those in maternal plasma for up to 12 hours following dosing. Exposure to TPI-derived radioactivity was higher in milk than in maternal plasma beginning 2 hours after dosing and continuing for at least 12 hours following administration of trifluridine/tipiracil.

8.3 Females and Males of Reproductive Potential

Pregnancy Testing

Verify pregnancy status in females of reproductive potential prior to initiating LONSURF [see Use in Specific Populations (8.1)].

Contraception

LONSURF can cause fetal harm when administered to a pregnant woman [see Use in Specific Populations (8.1)].

Females

Advise females of reproductive potential to use effective contraception during treatment with LONSURF and for at least 6 months after the final dose.

Males

Because of the potential for genotoxicity, advise males with female partners of reproductive potential to use condoms during treatment with LONSURF and for at least 3 months after the final dose [see Nonclinical Toxicology (13.1)].

8.4 Pediatric Use

Safety and effectiveness of LONSURF in pediatric patients have not been established.

Juvenile Animal Toxicity Data

Dental toxicity including whitening, breakage, and malocclusion (degeneration and disarrangement in the ameloblasts, papillary layer cells and odontoblasts) were observed in rats treated with trifluridine/tipiracil at doses ≥ 50 mg/kg (approximately 0.33 times the exposure at the clinical dose of 35 mg/m^2 twice daily).

8.5 Geriatric Use

Of the 1114 patients with metastatic colorectal cancer or gastric cancer who received single agent LONSURF in clinical studies, 45% were 65 years of age or over, and 11% were 75 and over. In the 246 patients who received LONSURF in combination with bevacizumab; 41% were 65 years of age or over, and 10% were 75 and over. While these studies were not designed to detect a difference in efficacy, no overall differences were observed in patients 65 or older versus younger patients with either LONSURF as a single agent or LONSURF in combination with bevacizumab.

Patients 65 years of age or older who received LONSURF as a single agent had a higher incidence of the following hematologic laboratory abnormalities compared to patients younger than 65 years: Grade 3 or 4 neutropenia (46% vs 32%), Grade 3 anemia (20% vs 14%), and Grade 3 or 4 thrombocytopenia (6% vs 3%). Patients 65 years of age or older who received LONSURF in combination with bevacizumab had a higher incidence of the following hematologic laboratory abnormalities compared to patients younger than 65 years: Grade 3 or 4 neutropenia (60% vs 46%) and Grade 3 or 4 thrombocytopenia (5% vs 4%).

8.6 Renal Impairment

No dose adjustment is recommended for patients with mild or moderate renal impairment (CLcr of 30 to 89 mL/min as determined by the Cockcroft-Gault formula). Reduce the dose of LONSURF for patients with severe renal impairment (CLcr of 15 to 29 mL/min) [see Dosage and Administration (2.3)]. The pharmacokinetics of trifluridine and tipiracil have not been studied in patients with end stage renal disease.

8.7 Hepatic Impairment

No adjustment to the starting dosage of LONSURF is recommended for patients with mild hepatic impairment. Do not initiate LONSURF in patients with baseline moderate or severe (total bilirubin >1.5 times ULN and any AST) hepatic impairment [see Clinical Pharmacology (12.3)].

11 DESCRIPTION

LONSURF contains trifluridine and tipiracil hydrochloride at a molar ratio of 1:0.5.

Trifluridine

Trifluridine, a nucleoside metabolic inhibitor, is described chemically as 2’-deoxy-5-(trifluoromethyl) uridine and has the following structural formula:

Trifluridine has a molecular formula C10H11F3N2O5 and a molecular weight of 296.20. Trifluridine is a white crystalline powder, soluble in water, ethanol, 0.01 mol/L hydrochloric acid, 0.01 mol/L sodium hydroxide solution; freely soluble in methanol, acetone; sparingly soluble in 2-propanol, acetonitrile; slightly soluble in diethyl ether; and very slightly soluble in isopropyl ether.

Tipiracil hydrochloride

Tipiracil hydrochloride, a thymidine phosphorylase inhibitor, is described chemically as 5-chloro-6-[(2-iminopyrrolidin-1-yl)methyl]pyrimidine-2,4-(1H,3H)-dione monohydrochloride or 2,4(1H,3H)-Pyrimidinedione, 5-chloro-6-[(2-imino-1-pyrrolidinyl)methyl]-, hydrochloride (1:1) and has the following structural formula:

Tipiracil hydrochloride has a molecular formula C9H11ClN4O2•HCl and a molecular weight of 279.12. Tipiracil hydrochloride is a white crystalline powder, soluble in water, 0.01 mol/L hydrochloric acid, and 0.01 mol/L sodium hydroxide; slightly soluble in methanol; very slightly soluble in ethanol; and practically insoluble in acetonitrile, 2-propanol, acetone, diisopropyl ether, and diethyl ether.

LONSURF (trifluridine and tipiracil) tablets for oral use contain 15 mg of trifluridine and 6.14 mg of tipiracil equivalent to 7.065 mg of tipiracil hydrochloride or 20 mg of trifluridine and 8.19 mg of tipiracil equivalent to 9.420 mg of tipiracil hydrochloride.

LONSURF tablets contain the following inactive ingredients: lactose monohydrate, pregelatinized starch, stearic acid, hypromellose, polyethylene glycol, titanium dioxide, ferric oxide, and magnesium stearate. The tablets are imprinted with ink containing shellac, ferric oxide red, ferric oxide yellow, titanium dioxide, FD&C Blue No. 2 Aluminum Lake, carnauba wax, and talc.

12 CLINICAL PHARMACOLOGY

12.1 Mechanism of Action

LONSURF consists of a thymidine-based nucleoside analog, trifluridine, and the thymidine phosphorylase inhibitor, tipiracil, at a molar ratio 1:0.5 (weight ratio, 1:0.471). Inclusion of tipiracil increases trifluridine exposure by inhibiting its metabolism by thymidine phosphorylase.

Following uptake into cancer cells, trifluridine is incorporated into DNA, interferes with DNA synthesis and inhibits cell proliferation. Trifluridine/tipiracil demonstrated anti-tumor activity against KRAS wild-type and mutant human colorectal cancer xenografts in mice.

12.2 Pharmacodynamics

Cardiac Electrophysiology

LONSURF administered to 42 patients with advanced solid tumors at the recommended dosage had no large effect (i.e. >20 ms) in the mean QTc interval when compared to placebo and no exposure-QT relationship was identified. Two of 42 patients (4.8%) had QTc >500 msec and 2.4% had a QTc increase from baseline >60 msec.

12.3 Pharmacokinetics

After twice daily dosing of LONSURF, systemic exposure (AUC) of trifluridine increased more than dose-proportionally over the dose range of 15 mg/m^2 (0.43 times the recommended dose) to 35 mg/m^2.

The accumulation of trifluridine was 3-fold for AUC0-12hr and 2-fold for Cmax at steady state while no accumulation was observed for tipiracil.

Administration of a single dose of LONSURF 35 mg/m^2 increased the mean AUC0-last of trifluridine by 37-fold and Cmax by 22-fold with reduced variability compared to administration of a single dose of trifluridine 35 mg/m^2 alone.

Absorption

Following a single oral administration of LONSURF at 35 mg/m^2 in patients with cancer, the mean time to peak plasma concentration (Tmax) of trifluridine was around 2 hours.

Food Effect

A standardized high-fat, high-calorie meal decreased trifluridine Cmax, tipiracil Cmax and AUC by approximately 40%, but did not change trifluridine AUC compared to those in a fasting state in patients with cancer following administration of a single dose of LONSURF 35 mg/m^2.

Distribution

Trifluridine mainly binds to human serum albumin. The in vitro protein binding of trifluridine in human plasma is >96%, independent of drug concentration and presence of tipiracil. Plasma protein binding of tipiracil is below 8%.

Elimination

After administration of LONSURF 35 mg/m^2, the mean elimination half-life (t1/2) of trifluridine was 1.4 hours and of tipiracil was 2.1 hours after a single dose. The mean elimination half-life at steady state of trifluridine was 2.1 hours and of tipiracil was 2.4 hours.

Metabolism

Trifluridine and tipiracil are not metabolized by cytochrome P450 (CYP) enzymes. Trifluridine is mainly eliminated by metabolism via thymidine phosphorylase to form an inactive metabolite, 5-(trifluoromethyl) uracil (FTY). No other major metabolites were detected in plasma or urine.

Excretion

After single oral administration of LONSURF (60 mg) with [^14C]-trifluridine, the total cumulative excretion of radioactivity was 60% of the administered dose. The majority of recovered radioactivity was eliminated into urine (55% of the dose) as FTY and trifluridine glucuronide isomers within 24 hours and the excretion into feces and expired air was <3% for both. The unchanged trifluridine was <3% of administered dose recovered in the urine and feces.

After single oral administration of LONSURF (60 mg) with [^14C]-tipiracil hydrochloride, recovered radioactivity was 77% of the dose, which consisted of 27% urinary excretion and 50% fecal excretion. Tipiracil was the major component and 6-HMU was the major metabolite in urine, and feces.

Specific Populations

Based on the population pharmacokinetic analysis, there is no clinically relevant effect of age, sex, or race (White or Asian) on the pharmacokinetics of trifluridine or tipiracil.

Patients with Renal Impairment

In a dedicated renal impairment study, all patients received LONSURF 35 mg/m^2 twice daily except for patients with severe renal impairment who received 20 mg/m^2 twice daily. Mild renal impairment (CLcr of 60 to 89 mL/min as determined by the Cockcroft-Gault formula) had no clinically important effect on steady-state AUC0-last of trifluridine and tipiracil. Moderate renal impairment (CLcr of 30 to 59 mL/min) increased steady-state AUC0-last of trifluridine by 56% and tipiracil by 139% compared to normal renal function (CLcr ≥ 90 mL/min). Severe renal impairment (CLcr of 15 to 29 mL/min) increased the dose-normalized steady-state AUC0-last of trifluridine by 140% and tipiracil by 614% compared to normal renal function. The pharmacokinetics of trifluridine and tipiracil have not been studied in patients with end stage renal disease.

Patients with Hepatic Impairment

No clinically important differences in the mean exposures of trifluridine and tipiracil were observed between patients with mild hepatic impairment (total bilirubin ≤ ULN and AST > ULN or total bilirubin <1 to 1.5 times ULN and any AST) to moderate hepatic impairment (total bilirubin >1.5 to 3 times ULN and any AST) and patients with normal hepatic function (total bilirubin and AST ≤ ULN); however, 5 of 6 patients with moderate hepatic impairment experienced Grade 3 or 4 increased bilirubin levels. The pharmacokinetics of trifluridine and tipiracil have not been studied in patients with severe hepatic impairment [see Dosage Modifications (2.2), Use in Specific Populations (8.6)].

Drug Interaction Studies

In vitro studies indicated that trifluridine, tipiracil, and FTY did not inhibit the CYP enzymes and had no inductive effect on CYP1A2, CYP2B6, or CYP3A4/5.

In vitro studies indicated that trifluridine was not an inhibitor of or substrate for human uptake and efflux transporters.

13 NONCLINICAL TOXICOLOGY

13.1 Carcinogenesis, Mutagenesis, Impairment of Fertility

No long-term studies evaluating the carcinogenic potential of trifluridine/tipiracil in animals have been performed. Trifluridine/tipiracil was genotoxic in a reverse mutation test in bacteria, a chromosomal aberration test in mammalian-cultured cells, and a micronucleus test in mice.

Animal studies did not indicate an effect of trifluridine/tipiracil on male fertility in rats. Dose-related increases in the corpus luteum count and implanted embryo count were observed, but female fertility was not affected.

14 CLINICAL STUDIES

14.1 Metastatic Colorectal Cancer

Previously treated metastatic colorectal cancer (single agent LONSURF)

RECOURSE

The efficacy of LONSURF was evaluated in RECOURSE (NCT01607957), an international, randomized, double-blind, placebo-controlled study conducted in patients with previously treated metastatic colorectal cancer (mCRC). Key eligibility criteria included prior treatment with at least 2 lines of standard chemotherapy for metastatic CRC, ECOG performance status (PS) 0-1, absence of brain metastasis, and absence of ascites requiring drainage in the past four weeks. Patients were randomized 2:1 to receive LONSURF 35 mg/m^2 or matching placebo orally twice daily after meals on Days 1-5 and 8-12 of each 28-day cycle until disease progression or unacceptable toxicity. Randomization was stratified by KRAS status (wild-type vs. mutant), time since diagnosis of first metastasis (<18 months vs. ≥ 18 months), and region (Japan vs. US, Europe and Australia). The major efficacy outcome measure was overall survival (OS) and an additional efficacy outcome measure was progression-free survival (PFS).

A total of 800 patients were randomized to LONSURF (N=534) with best supportive care (BSC) or matching placebo (N=266) plus BSC. The median age was 63 years, 61% were male, 58% and 35% were White and Asian respectively, and all patients had baseline ECOG PS of 0 or 1. The primary site of disease was colon (62%) or rectum (38%). KRAS status was wild-type (49%) or mutant (51%) at study entry. All patients received prior treatment with fluoropyrimidine-, oxaliplatin-, and irinotecan-based chemotherapy. All but one patient received bevacizumab and all but two patients with KRAS wild-type tumors received panitumumab or cetuximab.

Efficacy results are summarized in Table 9 and Figure 1.

Table 9: Efficacy Results from RECOURSE
 | LONSURF (N=534) | Placebo (N=266)
Overall Survival
Number of deaths, N (%) | 364 (68) | 210 (79)
Median OS (months) [Kaplan-Meier estimates] (95% CI) [Methodology of Brookmeyer and Crowley] | 7.1 (6.5, 7.8) | 5.3 (4.6, 6.0)
Hazard ratio (95% CI) | 0.68 (0.58, 0.81)
p-value [Stratified log-rank test (strata: KRAS status, time since diagnosis of first metastasis, region), 2-sided] | <0.001
Progression-Free Survival
Number of events, N (%) | 472 (88) | 251 (94)
Hazard ratio (95% CI) | 0.47 (0.40, 0.55)
p-value | <0.001

Figure 1: Kaplan-Meier Curves of Overall Survival in RECOURSE

Previously treated metastatic colorectal cancer (LONSURF in combination with bevacizumab)

SUNLIGHT

The efficacy of LONSURF in combination with bevacizumab was evaluated in SUNLIGHT (NCT 04737187), an international, randomized (1:1), open label study in patients with previously treated metastatic colorectal cancer. Patients were required to have received no more than 2 prior treatments for advanced disease, including a fluoropyrimidine, irinotecan, oxaliplatin, an anti-VEGF monoclonal antibody (optional) and an anti-EGFR monoclonal antibody for patients with RAS wild-type. Other key eligibility criteria included ECOG performance status (PS) 0-1, absence of symptomatic brain metastases, absence of ascites requiring drainage in the past 4 weeks, absence of uncontrolled hypertension, absence of non-healing wound, and absence of deep venous thromboembolic event in the past 4 weeks. Patients were randomized to receive LONSURF 35 mg/m^2 administered orally twice daily on Days 1 to 5 and 8 to 12 of each 28-day cycle with or without bevacizumab 5 mg/kg administered intravenously every 2 weeks (on Day 1 and Day 15) of each 4-week cycle until disease progression or unacceptable toxicity. Randomization was stratified by geographic region (North America, European Union, Rest of the World), time since diagnosis of metastatic disease (<18 months, ≥18 months) and RAS status (wild-type, mutant). The major efficacy outcome was overall survival (OS), and an additional efficacy outcome measure was progression-free survival (PFS).

A total of 492 patients were randomized to receive LONSURF in combination with bevacizumab (N=246) or LONSURF as a single agent (N=246). The trial population characteristics were as follows: median age 63 years, 52% male, 88% White, 1.4% Black, 0.2% Asian, 0.2% American Indian or Alaska Native, and 9.6% were unknown, 46% had ECOG PS 0 and 54% had ECOG PS 1. The primary site of disease was colon (73%) or rectum (27%). Seventy-one percent of patients had a RAS mutant status. A total of 92% of patients received 2 prior anticancer treatment regimens for advanced CRC; all patients received prior fluoropyrimidine; 99.8% of patients received prior irinotecan; 98% of patients received prior oxaliplatin. Among all 492 treated patients, 76% received prior anti-VEGF treatment, and 72% received an anti-VEGF monoclonal antibody. Among the 142 patients with RAS wild-type mCRC, 94% received prior anti-EGFR monoclonal antibody.

Efficacy results are summarized in Table 10 and Figure 2.

Table 10: Efficacy Results from SUNLIGHT
 | LONSURF plus Bevacizumab (N=246) | LONSURF (N=246)
Overall survival
Number of deaths, N (%) | 148 (60) | 183 (74)
Median OS (months) [Kaplan-Meier estimates] (95% CI) [Methodology of Brookmeyer and Crowley] | 10.8 (9.4, 11.8) | 7.5 (6.3, 8.6)
Hazard ratio (95% CI) [Stratified proportional hazards model (strata: region, time since first metastasis diagnosis, RAS status)] | 0.61 (0.49, 0.77)
p-value [Stratified log-rank test (strata: region, time since first metastasis diagnosis, RAS status), 1-sided p-value] | <0.001
Progression-free survival (per investigator)
Number of events N (%) | 206 (84) | 236 (96)
Median PFS (months) (95% CI) | 5.6 (4.5, 5.9) | 2.4 (2.1, 3.2)
Hazard ratio (95% CI) | 0.44 (0.36, 0.54)
p-value | <0.001

Figure 2: Kaplan-Meier Curves of Overall Survival in SUNLIGHT

14.2 Metastatic Gastric Cancer

The efficacy of LONSURF was evaluated in TAGS (NCT02500043), an international, randomized, double-blind, placebo-controlled study in patients with metastatic gastric or gastroesophageal junction (GEJ) adenocarcinoma previously treated with at least 2 prior regimens for advanced disease. Previous treatments must have included a fluoropyrimidine, a platinum, and either a taxane or irinotecan. Patients with HER2/neu-positive tumors must have received prior HER2/neu-targeted therapy, if available. Adjuvant chemotherapy could be counted as one prior regimen in patients who had recurrence during or within 6 months of completion of the adjuvant chemotherapy. Other key eligibility criteria included ECOG performance status (PS) 0 or 1. Patients were randomized 2:1 to receive LONSURF 35 mg/m^2 orally twice daily on Days 1-5 and 8-12 of each 28-day cycle with best supportive care (BSC) or matching placebo with BSC until disease progression or unacceptable toxicity. Randomization was stratified by ECOG PS at baseline (0 vs. 1), prior ramucirumab (yes vs. no), and geographic region (Japan vs. rest of world). The major efficacy outcome measure was OS and an additional outcome measure was PFS.

A total of 507 patients were randomized to LONSURF (N=337) or placebo (N=170). The median age was 63 years, 73% were male, 70% and 16% were White and Asian respectively, and 38% had a baseline ECOG PS of 0. Seventy-one percent of patients had gastric tumors, 29% had GEJ tumors, and two patients had gastric/GEJ tumors. All patients received platinum-based chemotherapy, 99% received fluoropyrimidine-based therapy, 91% received a taxane, 55% received irinotecan, and 33% received ramucirumab. The HER2 status was negative in 62%, positive in 19%, and unknown in 20% of patients. Among the 94 patients with HER2 positive tumors, 89% received prior anti-HER2 therapy.

Efficacy results are summarized in Table 11 and Figure 3.

Table 11: Efficacy Results from TAGS
 | LONSURF (N=337) | Placebo (N=170)
Overall Survival
Number of deaths, N (%) | 244 (72) | 140 (82)
Median OS (months) [Kaplan-Meier estimates] (95% CI) [Methodology of Brookmeyer and Crowley] | 5.7 (4.8, 6.2) | 3.6 (3.1, 4.1)
Hazard ratio (95% CI) | 0.69 (0.56, 0.85)
p-value [Stratified log-rank test (strata: ECOG PS, prior ramucirumab treatment, region), 2-sided] | 0.0006
Progression-Free Survival
Number of events, N (%) | 287 (85) | 156 (92)
Hazard ratio (95% CI) | 0.56 (0.46, 0.68)
p-value | <0.0001

Figure 3: Kaplan-Meier Curves of Overall Survival in TAGS

15 REFERENCES

1. “OSHA Hazardous Drugs”. OSHA. http://www.osha.gov/SLTC/hazardousdrugs/index.html

16 HOW SUPPLIED/STORAGE AND HANDLING

LONSURF 15 mg/6.14 mg tablets are supplied as white, biconvex, round, film-coated tablet, imprinted with ‘15’ on one side, and ‘102’ and ’15 mg’ on the other side, in gray ink. The tablets are packaged in HDPE bottles with child resistant closures in the following presentations:

- 20 count: NDC 64842-1025-1
- 40 count: NDC 64842-1025-2
- 60 count: NDC 64842-1025-3

LONSURF 20 mg/8.19 mg tablets are supplied as pale red, biconvex, round, film-coated tablet, imprinted with ‘20’ on one side, and ‘102’ and ‘20 mg’ on the other side, in gray ink. The tablets are packaged in HDPE bottles with child resistant closures in the following presentations:

- 20 count: NDC 64842-1020-1
- 40 count: NDC 64842-1020-2
- 60 count: NDC 64842-1020-3

Store at 20°C to 25°C (68°F to 77°F); excursions are permitted from 15°C to 30°C (59°F to 86°F) [See USP Controlled Room Temperature].

LONSURF is a cytotoxic drug. Follow applicable special handling and disposal procedures.^1

If stored outside of original bottle, discard after 30 days.

17 PATIENT COUNSELING INFORMATION

Advise the patient to read the FDA-approved patient labeling (Patient Information).

Severe Myelosuppression

Advise patients to immediately contact their healthcare provider if they experience signs or symptoms of infection and advise patients to keep all appointments for blood tests [see Warnings and Precautions (5.1)].

Gastrointestinal Toxicity

Advise patients to contact their healthcare provider for severe or persistent nausea, vomiting, diarrhea, or abdominal pain [see Adverse Reactions (6.1)].

Administration Instructions

Advise patients that LONSURF is available in two strengths and they may receive both strength tablets to provide the prescribed dosage.

Advise patients to take LONSURF with food [see Dosage and Administration (2.1)].

Advise patients not to retake doses of LONSURF that are vomited or missed and to continue with the next scheduled dose.

Advise patients that anyone else who handles their medication should wear gloves [see References (15)].

Embryo-Fetal Toxicity

Advise pregnant women and females of reproductive potential of the potential risk to the fetus. Advise females to inform their healthcare provider of a known or suspected pregnancy [see Warnings and Precautions (5.2), Use in Specific Populations (8.3)].

Advise female patients of reproductive potential to use effective contraception during treatment with LONSURF and for at least 6 months after the final dose [see Warnings and Precautions (5.2), Use in Specific Populations (8.3)].

Advise males with female partners of reproductive potential to use condoms during treatment with LONSURF and for at least 3 months after the final dose [see Use in Specific Populations (8.3), Nonclinical Toxicology (13.1)].

Lactation

Advise women not to breastfeed during treatment with LONSURF and for 1 day following the final dose [see Use in Specific Populations (8.2)].

Manufactured by: Taiho Pharmaceutical Co., Ltd., Japan
Manufactured for: Taiho Oncology, Inc., Princeton, NJ 08540 USA

LONSURF is a registered trademark of Taiho Pharmaceutical Co., Ltd. used under license by
Taiho Oncology, Inc.

PATIENT INFORMATION
LONSURF® (LON-serf)
(trifluridine and tipiracil)
tablets

What is the most important information I should know about LONSURF?
Your healthcare provider should do blood tests before you receive LONSURF, at day 15 during treatment with LONSURF, and as needed to check your blood cell counts.
LONSURF may cause serious side effects, including:
Low blood cell counts. Low blood counts are common with LONSURF and can sometimes be severe and life-threatening. LONSURF can cause a decrease in your white blood cells, red blood cells, and platelets. Low white blood cells can make you more likely to get serious infections that could lead to death. Your healthcare provider may:

- lower your dose of LONSURF or stop LONSURF if you have low white blood cell or low platelet counts.

Tell your healthcare provider right away if you get any of the following signs and symptoms of infection during treatment with LONSURF:

- fever
- chills
- body aches

See “What are the possible side effects of LONSURF?” for more information about side effects.

What is LONSURF?
LONSURF is a prescription medicine used:

- alone or in combination with the medicine bevacizumab to treat adults with colorectal cancer:
  - that has spread to other parts of the body, and
  - who have been previously treated with certain chemotherapy medicines.
- alone to treat adults with a kind of stomach cancer called gastric cancer including adenocarcinoma of the gastroesophageal junction:
  - that has spread to other parts of the body, and
  - who have been previously treated with at least 2 types of treatment which included certain medicines.

It is not known if LONSURF is safe and effective in children.

Before you take LONSURF, tell your healthcare provider about all of your medical conditions, including if you:

- have kidney or liver problems
- are pregnant or plan to become pregnant. LONSURF can harm your unborn baby.
  For females who can become pregnant:
  - Your healthcare provider will do a pregnancy test before you start treatment with LONSURF.
  - You should use effective birth control during treatment with LONSURF and for at least 6 months after your last dose of LONSURF. (Talk to healthcare provider about methods of birth control that can be used during this time)
  - Tell your healthcare provider right away if you become pregnant.
  For males:
  - You should use a condom during sex with female partners who are able to become pregnant during your treatment with LONSURF and for 3 months after your last dose of LONSURF. Tell your healthcare provider right away if your partner becomes pregnant while you are taking LONSURF.

- are breastfeeding or plan to breastfeed. It is not known if LONSURF passes into breast milk. Do not breastfeed during treatment with LONSURF and for 1 day after your last dose of LONSURF.

Tell your healthcare provider about all the medicines you take, including prescription and over-the-counter medicines, vitamins, and herbal supplements.

How should I take LONSURF?

- Take LONSURF exactly as your healthcare provider tells you.
  LONSURF comes in two strengths. Your healthcare provider may prescribe both strengths for your prescribed dose.
- Take LONSURF 2 times a day with food.
- Swallow LONSURF tablets whole.
- Your caregiver should wear gloves when handling LONSURF tablets.
- If you vomit right after taking a dose, or miss a dose of LONSURF, do not take additional doses to make up for the vomited or missed dose. Call your healthcare provider for instructions about what to do for a missed dose.
- Wash your hands after handling the LONSURF tablets.

What are the possible side effects of LONSURF?
LONSURF may cause serious side effects, including:

- See “What is the most important information I should know about LONSURF?”

The most common side effects of LONSURF when used alone include:

- low blood counts
- tiredness and weakness
- nausea
- decreased appetite

- diarrhea
- vomiting
- stomach-area (abdominal) pain
- fever

The most common side effects of LONSURF when used in combination with bevacizumab include:

- low blood counts
- tiredness and weakness
- nausea
- certain abnormal liver function blood tests

- decreased salt (sodium) in your blood
- diarrhea
- stomach-area (abdominal) pain
- decreased appetite

Tell your healthcare provider if you have nausea, vomiting, or diarrhea that is severe or that does not go away.
These are not all of the possible side effects of LONSURF. For more information, ask your healthcare provider.
Call your doctor for medical advice about side effects. You may report side effects to FDA at 1-800-FDA-1088.

How should I store LONSURF?

- Store LONSURF at room temperature between 68°F and 77°F (20°C and 25°C).
- If you store LONSURF outside of the original bottle, throw away (dispose of) any unused LONSURF tablets after 30 days.
- Talk to your healthcare provider about how to safely dispose of LONSURF.

Keep LONSURF and all medicines out of the reach of children.

General information about the safe and effective use of LONSURF
Medicines are sometimes prescribed for purposes other than those listed in a Patient Information leaflet. Do not use LONSURF for a condition for which it was not prescribed. Do not give LONSURF to other people, even if they have the same symptoms that you have. It may harm them. If you would like more information, talk to your healthcare provider. You can ask your pharmacist or healthcare provider for information about LONSURF that is written for health professionals.

What are the ingredients in LONSURF?
Active ingredients: trifluridine and tipiracil hydrochloride
Other ingredients: lactose monohydrate, pregelatinized starch, stearic acid, hypromellose, polyethylene glycol, titanium dioxide, ferric oxide, and magnesium stearate
Imprinting ink: shellac, ferric oxide red, ferric oxide yellow, titanium dioxide, FD&C Blue No. 2 Aluminum Lake, carnauba wax, and talc.
Manufactured by: Taiho Pharmaceutical Co., Ltd., Japan
Manufactured for: Taiho Oncology, Inc., Princeton, NJ 08540 USA
LONSURF is a registered trademark of Taiho Pharmaceutical Co., Ltd. used under license by Taiho Oncology, Inc.
For more information, go to www.Lonsurf.com or call 1-844-878-2446.

This Patient Information has been approved by the U.S. Food and Drug Administration.

Revised: 8/2023

PRINCIPAL DISPLAY PANEL

NDC 64842-1025-1

Lonsurf®
(trifluridine and tipiracil*) tablets

15 mg/6.14 mg*

20 tablets

Rx only

NDC 64842-1025-1

Lonsurf®
(trifluridine and tipiracil*) tablets

15 mg/6.14 mg*

For oral administraion
20 tablets

Rx only

NDC 64842-1025-2

Lonsurf®
(trifluridine and tipiracil*) tablets

15 mg/6.14 mg*

40 tablets

Rx only

NDC 64842-1025-2

Lonsurf®
(trifluridine and tipiracil*) tablets

15 mg/6.14 mg*

For oral administraion
40 tablets

Rx only

NDC 64842-1025-3

Lonsurf®
(trifluridine and tipiracil*) tablets

15 mg/6.14 mg*

60 tablets

Rx only

NDC 64842-1025-3

Lonsurf®
(trifluridine and tipiracil*) tablets

15 mg/6.14 mg*

For oral administraion
60 tablets

Rx only

NDC 64842-1020-1

Lonsurf®
(trifluridine and tipiracil*) tablets

20 mg/8.19 mg*

20 tablets

Rx only

NDC 64842-1020-1

Lonsurf®
(trifluridine and tipiracil*) tablets

20 mg/8.19 mg*

For oral administraion
20 tablets

Rx only

NDC 64842-1020-2

Lonsurf®
(trifluridine and tipiracil*) tablets

20 mg/8.19 mg*

40 tablets

Rx only

NDC 64842-1020-2

Lonsurf®
(trifluridine and tipiracil*) tablets

20 mg/8.19 mg*

For oral administraion
40 tablets

Rx only

NDC 64842-1020-3

Lonsurf®
(trifluridine and tipiracil*) tablets

20 mg/8.19 mg*

60 tablets

Rx only

NDC 64842-1020-3

Lonsurf®
(trifluridine and tipiracil*) tablets

20 mg/8.19 mg*

For oral administraion
60 tablets

Rx only